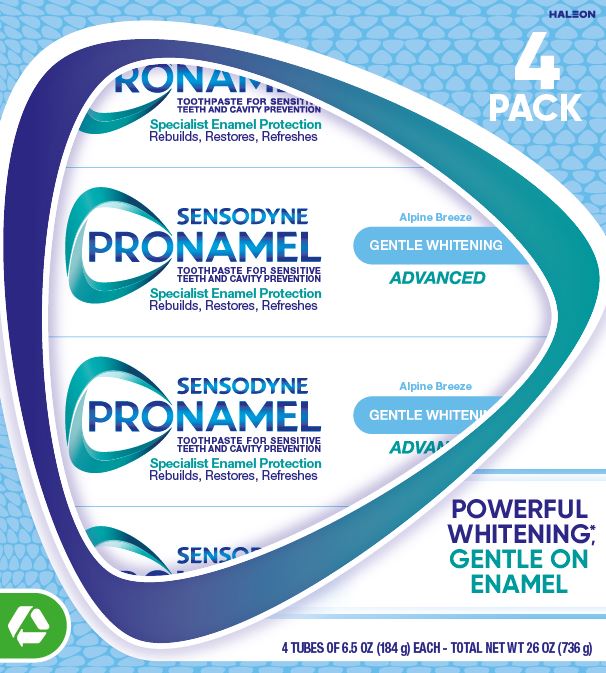 DRUG LABEL: Sensodyne Pronamel
NDC: 0135-0580 | Form: PASTE
Manufacturer: Haleon US Holdings LLC
Category: otc | Type: HUMAN OTC DRUG LABEL
Date: 20240904

ACTIVE INGREDIENTS: POTASSIUM NITRATE 50 mg/1 g; SODIUM FLUORIDE 1.15 mg/1 g
INACTIVE INGREDIENTS: WATER; HYDRATED SILICA; SORBITOL; GLYCERIN; POLYETHYLENE GLYCOL 400; COCAMIDOPROPYL BETAINE; XANTHAN GUM; TITANIUM DIOXIDE; SACCHARIN SODIUM; SODIUM HYDROXIDE

Drug Facts

Active ingredients

Potassium nitrate 5%

Sodium fluoride 0.25% (0.15% w/v fluoride ion)

Purposes

Antihypersensitivity

Anticavity

Uses

- builds increasing protection against painful sensitivity of the teeth to cold, heat, acids, sweets, or contact.
- aids in the prevention of dental cavities.

Warnings

Stop use and ask a dentist if

- the problem persists or worsens. Sensitive teeth may indicate a serious problem that may need prompt care by a dentist.
- pain/sensitivity still persists after 4 weeks of use.

Keep out of reach of children

If more than used for brushing is accidentally swallowed, get medical help or contact a Poison Control Center right away.

Directions

- adults and children 12 years of age and older:
- apply at least a 1-inch strip of the product onto a soft bristle toothbrush.
- brush teeth thoroughly for at least 1 minute twice a day (morning and evening), and not more than 3 times a day, or as recommended by a dentist or doctor. Make sure to brush all sensitive areas of the teeth. Minimize swallowing. Spit out after brushing.
- children under 12 years of age: Consult a dentist or doctor.

Other information

- do not store above 25°C (77°F)

Inactive ingredients

water, hydrated silica, sorbitol, glycerin, PEG-8, cocamidopropyl betaine, flavor, xanthan gum, titanium dioxide, sodium saccharin, sodium hydroxide

Questions or comments?

1-866-844-2797

Generic Section

SENSODYNE PRONAMEL

Healthy white teeth start with strong enamel.

Pronamel has a proven specialist technology that has been developed to maximize the effect of fluoride on enamel.

ACID ATTACKS ENAMEL

WEAKENING THE ENAMEL STRUCTURE

PRONAMEL REBUUILDS & RESTORES ENAMEL

FOR STRONG HEALTHY TEETH

Does not contain: SLS/sulfates • artificial dyes • parabens • triclosan • peroxide

* removes stains

ALWAYS FOLLOW THE LABEL

CARTON RECYCLE

TUBE RECYCLE

CAP† CHECK LOCALLY

† Recycling facilities for the cap may not exist in your area

Save Water

Turn off tap while brushing

Recyclable Packaging

Recyclable Carton

Recyclable Tube & Cap†

SPECIALIST ENAMEL PROTECTION

The acids in your diet can damage tooth enamel, leading to dull, yellow teeth.

Wine Acids

Fruit Acids

Soda Acids

Pronamel strengthens acid weakened enamel and protects teeth from these acids, keeping teeth strong, healthy and white.

SENSODYNE PRONAMEL

POWERFUL WHITENING*

GENTLE ON ENAMEL

#1 DENTIST RECOMMENDED ENAMEL BRAND

Principal Display Panel

4 PACK

SENSODYNE PRONAMEL

TOOTHPASTE FOR SENSITIVE TEETH AND CAVITY PREVENTION

Specialist Enamel Protection

Rebuilds, Restores, Refreshes

Alpine Breeze

GENTLE WHITENING

ADVANCED

POWERFUL WHITENING*,

GENTLE ON ENAMEL

4 TUBES OF 6.5 OZ (184 g) EACH – TOTAL NET WT 26 OZ (736 g)